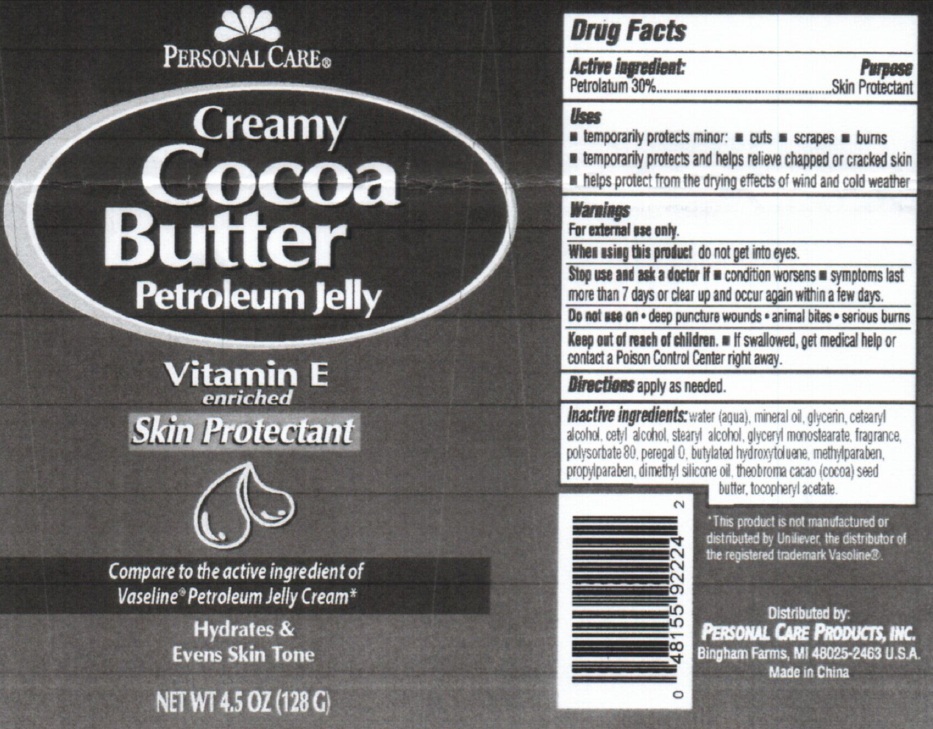 DRUG LABEL: Creamy Cocoa Butter Petroleum Jelly
                        
NDC: 29500-2224 | Form: CREAM
Manufacturer: Personal Care Products, LLC
Category: otc | Type: HUMAN OTC DRUG LABEL
Date: 20111230

ACTIVE INGREDIENTS: PETROLATUM 30 g/100 g
INACTIVE INGREDIENTS: WATER; MINERAL OIL; GLYCERIN; CETOSTEARYL ALCOHOL; STEARYL ALCOHOL; GLYCERYL MONOSTEARATE; POLYSORBATE 80; POLYOXYL 20 CETOSTEARYL ETHER; BUTYLATED HYDROXYTOLUENE; METHYLPARABEN; PROPYLPARABEN; COCOA BUTTER; .ALPHA.-TOCOPHEROL ACETATE, DL-

CREAMY COCOA BUTTER PETROLEUM JELLY

Active Ingredient

Petrolatum 30%

Purpose

Skin protectant

Uses

Temporarily protects minor cuts, scrapes, burns

Temporarily protects and helps relieve chapped or cracked skin

helps protect from the drying effects of wind and cold weather.

Warnings

For external use only

When using this product do not get into eyes.

Stop use and ask a doctor if condition worsens

symptoms last more than 7 days or clear up and occur again within a few days.

Do not use on deep puncture wounds

animal bites

serious burns

Keep out of reach of children.

If swallowed, get medical help or contact a Poison Control Center right away.

DOSAGE AND ADMINISTRATION

Directions apply as needed.

Inactive ingredients:

Water (aqua), mineral oil, glycerin, cetearl alcohol, cetyl alcohol, stearyl alcohol, glyceryl monostearate, fragrance, polysorbate 80, peregal O, butylated hydroxytoluene, methlparaben, propylparaben, dimethyl silicone oil, theobroma cacao (cocoa) seed butter, tocopheryl acetate

PACKAGE LABEL

Personal Care

Creamy Cocoa Butter Petroleum Jelly

Vitamin E

enriched

Skin Protectant

Compare to the active ingredient of Vaseline Petroleum Jelly Cream

Hydrates and Evens Skin Tone

NET WT 4.5 oz (128G)

DESCRIPTION

This product is not manufactured or distributed by Unilever, the distributor of the registered trademark Vasoline

Distributed by

Personal Care Products, Inc.

Bingham Farms, MI 48025-2463 USA

Made In China